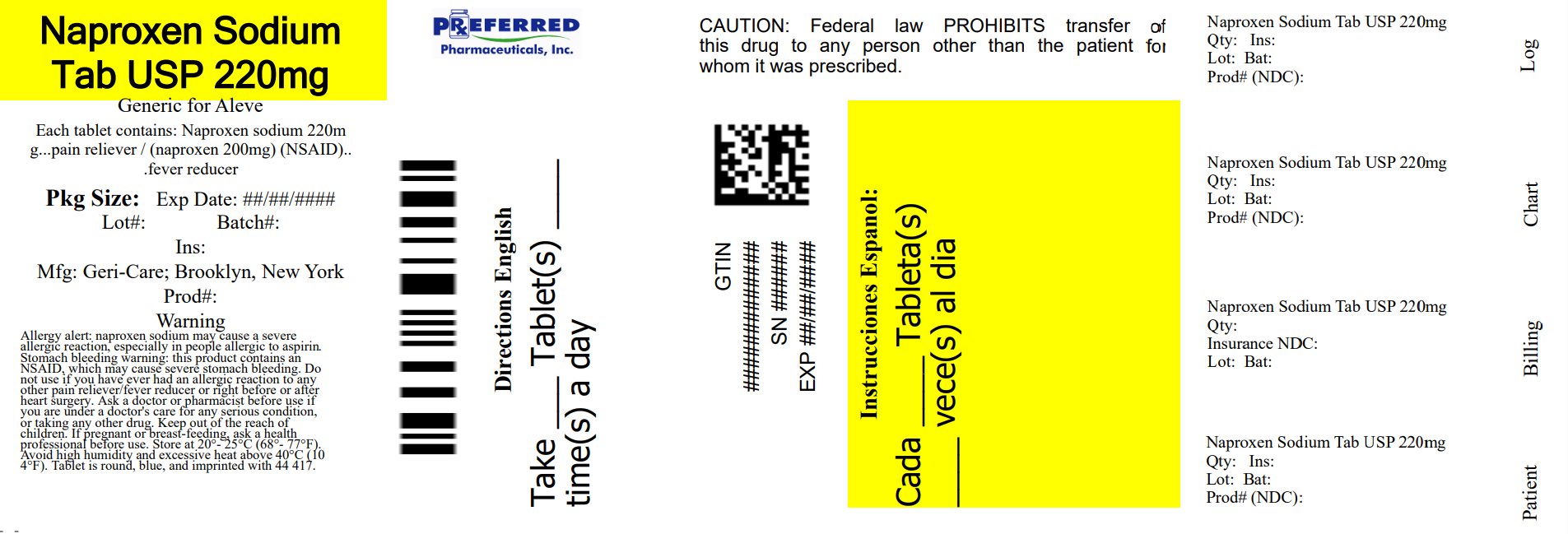 DRUG LABEL: Naproxen
NDC: 68788-7572 | Form: TABLET
Manufacturer: Preferred Pharmaceuticals, Inc.
Category: otc | Type: HUMAN OTC DRUG LABEL
Date: 20250818

ACTIVE INGREDIENTS: NAPROXEN SODIUM 220 mg/1 1
INACTIVE INGREDIENTS: SILICON DIOXIDE; CROSCARMELLOSE SODIUM; FD&C BLUE NO. 2; POLYVINYL ALCOHOL, UNSPECIFIED; MAGNESIUM STEARATE; MICROCRYSTALLINE CELLULOSE; POLYETHYLENE GLYCOL, UNSPECIFIED; POVIDONE, UNSPECIFIED; TITANIUM DIOXIDE; TALC

gc 951-954L

Active ingredient (in each tablet)

Naproxen sodium 220 mg
(Naproxen 200 mg) (NSAID)*

*nonsteroidal anti-inflammatory drug

Purpose

Pain reliever/ fever reducer

Uses

temporarily relieves minor aches and pain due to:

- backache
- muscular aches
- minor pain of arthritis
- menstrual cramps
- headache
- toothache
- the common cold

temporarily reduces fever

Warnings

Allergy alert: Naproxen sodium may cause a severe allergic reaction, especially in people allergic to aspirin. Symptoms may include:

- hives
- facial swelling
- asthma (wheezing)
- shock
- skin reddening
- rash
- blisters

If an allergic reaction occurs, stop use and seek medical help right away.

Stomach bleeding warning: This product contains an NSAID, which may cause severe stomach bleeding. The chance is higher if you:

- are age 60 or older
- have had stomach ulcers or bleeding problems
- take a blood thinning (anticoagulant) or steroid drug
- take other drugs containing prescription or nonprescription NSAIDs (aspirin, ibuprofen, naproxen, or others)
- have 3 or more alcoholic drinks every day while using this product.
- take more or for a longer time than directed.

Heart attack and stroke warning: NSAIDs, except aspirin, increase the risk of heart attack, heart failure, and stroke. These can be fatal. The risk is higher if you use more than directed or for longer than directed.

Do not use

- if you have ever had an allergic reaction to any other pain reliever / fever reducer
- right before or after heart surgery

Ask a doctor before use if

- the stomach bleeding warning applies to you
- you have a history of stomach problems such as heartburn
- you have high blood pressure, heart disease, liver cirrhosis, kidney disease, asthma, or had a stroke
- you are taking a diuretic
- you have problems or serious side effects from taking pain relievers or fever reducers

Ask a doctor or pharmacist before use if

- under a doctor's care for any serious condition
- taking any other drug

When using this product

- take with food or milk if stomach upset occurs

Stop use and ask doctor if

- you experience any of the following signs of stomach bleeding:
  - feel faint
  - vomit blood
  - have bloody or black stools
  - have a stomach pain that dose not get better
- you have symptoms of heart problems or stroke

 leg swelling  chest pain
 slurred speech  trouble breathing
 weakness in one part or side of body

- pain gets worse or lasts more than 10 days
- fever gets worse or lasts more than 3 days
- you have difficulty swallowing
- it feels like the pill is stuck in your throat
- redness or swelling is present in the painful area
- any new symptoms appear

PREGNANCY OR BREAST FEEDING

If pregnant or breast-feeding, ask a health professional
before use. It is especially important not to use naproxen
sodium during the last 3 months of pregnancy unless definitely
directed to do so by a doctor because it may cause problems in
the unborn child or complications during delivery.

Keep out of reach of children. In case of overdose, get medical help or contact a Poison Control Center (1-800-222-1222) right away.

Directions

- do not take more than directed
- the smallest effective dose should be used
- drink a full glass of water with each dose
- adults and children 12 years and older
- take 1 tablet every 8 to 12 hours while symptoms last
- for the first dose you may take 2 tablets within the first hour
- do not exceed 2 tablets in any 8 to 12 hour period
- do not exceed 3 tablets in a 24 hour period
- children under 12 years: ask a doctor

Storage

- Store at 20-25 oC (68-77 oF). Avoid high humidity and excessive heat above 40 ^0C (104 ^0F)

Other information

- each tablet contains: sodium 220 mg
NDC 68788-7582-02 Bottle of 20
  NDC 68788-7582-03 Bottle of 30
  NDC 68788-7582-04 Bottle of 40
  NDC 68788-7582-06 Bottle of 60

Repackaged by Preferred Pharmaceuticals, Inc.

Inactive ingredients

croscarmellose sodium, FD&C blue #2 aluminum lake, magnesium stearate, microcrystalline cellulose, polyethylene glycol, polyvinyl
alcohol, povidone, silicon dioxide, talc, titanium dioxide

Questions or comments?

Call 1-800-540-3765